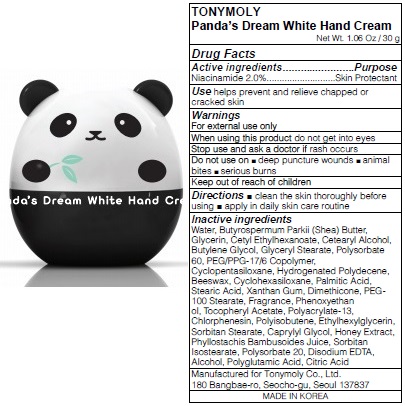 DRUG LABEL: TONYMOLY PANDAS DREAM WHITE HAND
NDC: 59078-220 | Form: CREAM
Manufacturer: TONYMOLY CO.,LTD
Category: otc | Type: HUMAN OTC DRUG LABEL
Date: 20160120

ACTIVE INGREDIENTS: Niacinamide 0.6 g/30 g
INACTIVE INGREDIENTS: Water; SHEA BUTTER

ACTIVE INGREDIENT

Active ingredients: Niacinamide 2.0%

INACTIVE INGREDIENT

Inactive ingredients: Water, Butyrospermum Parkii (Shea) Butter, Glycerin, Cetyl Ethylhexanoate, Cetearyl Alcohol, Butylene Glycol, Glyceryl Stearate, Polysorbate 60, PEG/PPG-17/6 Copolymer, Cyclopentasiloxane, Hydrogenated Polydecene, Beeswax, Cyclohexasiloxane, Palmitic Acid, Stearic Acid, Xanthan Gum, Dimethicone, PEG-100 Stearate, Fragrance, Phenoxyethan ol, Tocopheryl Acetate, Polyacrylate-13, Chlorphenesin, Polyisobutene, Ethylhexylglycerin, Sorbitan Stearate, Caprylyl Glycol, Honey Extract, Phyllostachis Bambusoides Juice, Sorbitan Isostearate, Polysorbate 20, Disodium EDTA, Alcohol, Polyglutamic Acid, Citric Acid

PURPOSE

Purpose: Skin Protectant

WARNINGS

Warnings: For external use only

When using this product do not get into eyes

Stop use and ask a doctor if rash occurs

Do not use on - deep puncture wounds - animal bites - serious burns

Keep out of reach of children

KEEP OUT OF REACH OF CHILDREN

Use

Use: helps prevent and relieve chapped or cracked skin

Directions

Directions: - clean the skin thoroughly before using - apply in daily skin care routined